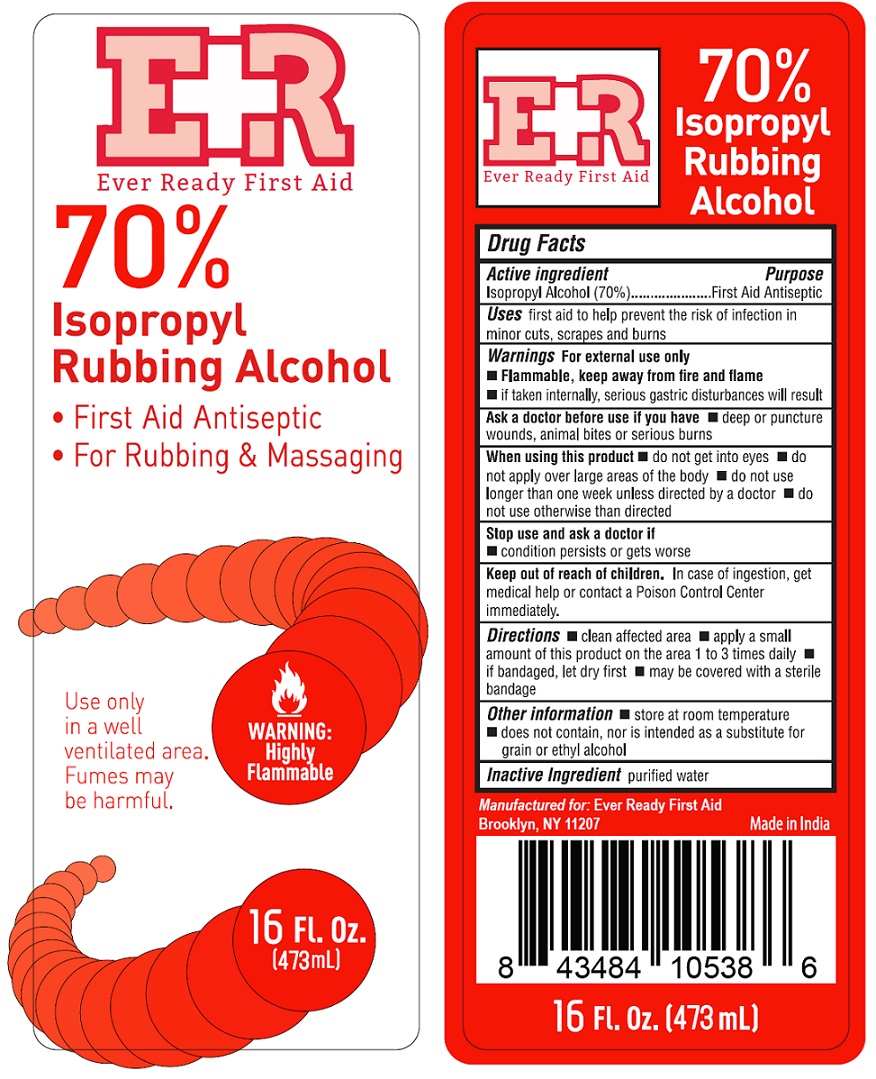 DRUG LABEL: 70% Isopropyl Rubbing Alcohol
NDC: 72976-001 | Form: LIQUID
Manufacturer: SZY Holdings, LLC dba EverReady First Aid
Category: otc | Type: HUMAN OTC DRUG LABEL
Date: 20241218

ACTIVE INGREDIENTS: ISOPROPYL ALCOHOL 70 mL/100 mL
INACTIVE INGREDIENTS: WATER

70% Isopropyl Rubbing Alcohol

Active Ingredient (by volume)

Isopropyl Alcohol (70%)

Purpose

First Aid Antiseptic

Uses

- first aid to help prevent the risk of infection in minor cuts, scrapes and burns

Warnings

For external use only

- Flammable, keep away from fire and flame
- if taken internally, serious gastric disturbances will result

Ask a doctor before use if you have

- deep or puncture wounds, animal bites or serious burns

When using this product

- do not get into eyes
- do not apply over large areas of the body
- do not use longer than one week unless directed by a doctor
- do not use otherwise than directed

Stop use and ask a doctor if

- condition persists or gets worse

Keep out of reach of children

In case of ingestion, get medical help or contact a Poison Control Center immediately.

Directions

- clean effected area
- apply a small amount of this product on the area 1 to 3 times daily
- if bandaged, let dry first
- may be covered with a sterile bandage

Other information

- store at room temperature
- does not contain, nor is intended as a substitute for grain or ethyl alcohol

Inactive Ingredient

Purified Water

PACKAGE LABEL

PRINCIPAL DISPLAY PANEL

70% ISOPROPYL RUBBING ALCOHOL
FIRST AID ANTISEPTIC
16 FL.OZ (473 mL)